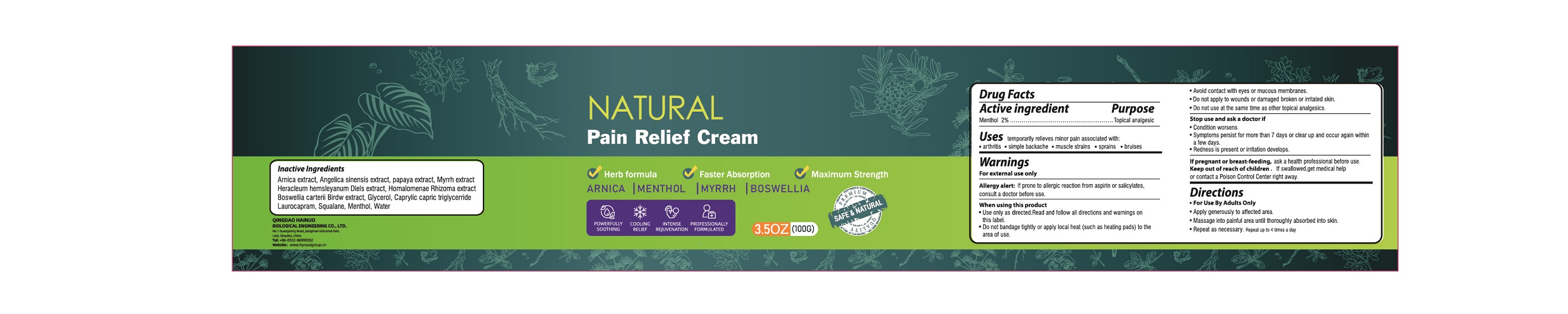 DRUG LABEL: Pain Relief Cream
NDC: 78149-205 | Form: SOLUTION
Manufacturer: QINGDAO HAINUO BIOLOGICAL ENGINEERING CO., LTD.
Category: otc | Type: HUMAN OTC DRUG LABEL
Date: 20231213

ACTIVE INGREDIENTS: MENTHOL 2 g/100 g
INACTIVE INGREDIENTS: ARNICA MONTANA FLOWER; ANGELICA SINENSIS ROOT; PAPAYA; MYRRH; HERACLEUM HEMSLEYANUM WHOLE; HOMALOMENA OCCULTA ROOT; BOSWELLIA SACRA WHOLE; GLYCERIN; MEDIUM-CHAIN TRIGLYCERIDES; LAUROCAPRAM; SQUALANE; WATER

Pain Relief Cream

Active Ingredient

Menthol 2%

Purpose

Topical analgesic

Use

temporarily relieves minor pain associated with:

- arthritis
- simple backache
- muscle strains
- sprains
- bruises

Warnings

For external use only

Allergy alert:If prone to allergic reaction from aspirin or salicylates,consult a doctor before use.

Do not use

- Do not bandage tightly or aooly local heat (such as heating pads) to the aera of use.
- Avoid contact with eyes or mucous membranes.
- Do not apply to wounds or damaged broken or irritated skin.
- Do not use at the same time as other topical analgesics.

WHEN USING

Use only as directed.Read and follow all directions and warmings on this label.

If pregnant or breast-feeding,ask a health professional before use.

Stop use and ask a doctor if

- Condition worsens
- Symptoms persist for more than 7 days or clear up and occur again within a few days.
- Redness is present or irritation develops.

Keep out of reach of children. If swallowed,get medical help or contact a Poison Contriol Center right away.

Directions

- For Use By Adults Only
- Apply generously to affected area.
- Massage into painful area until thoroughly absorbed into skin
- Repeat as necessary.Repeat up 4 times a day.